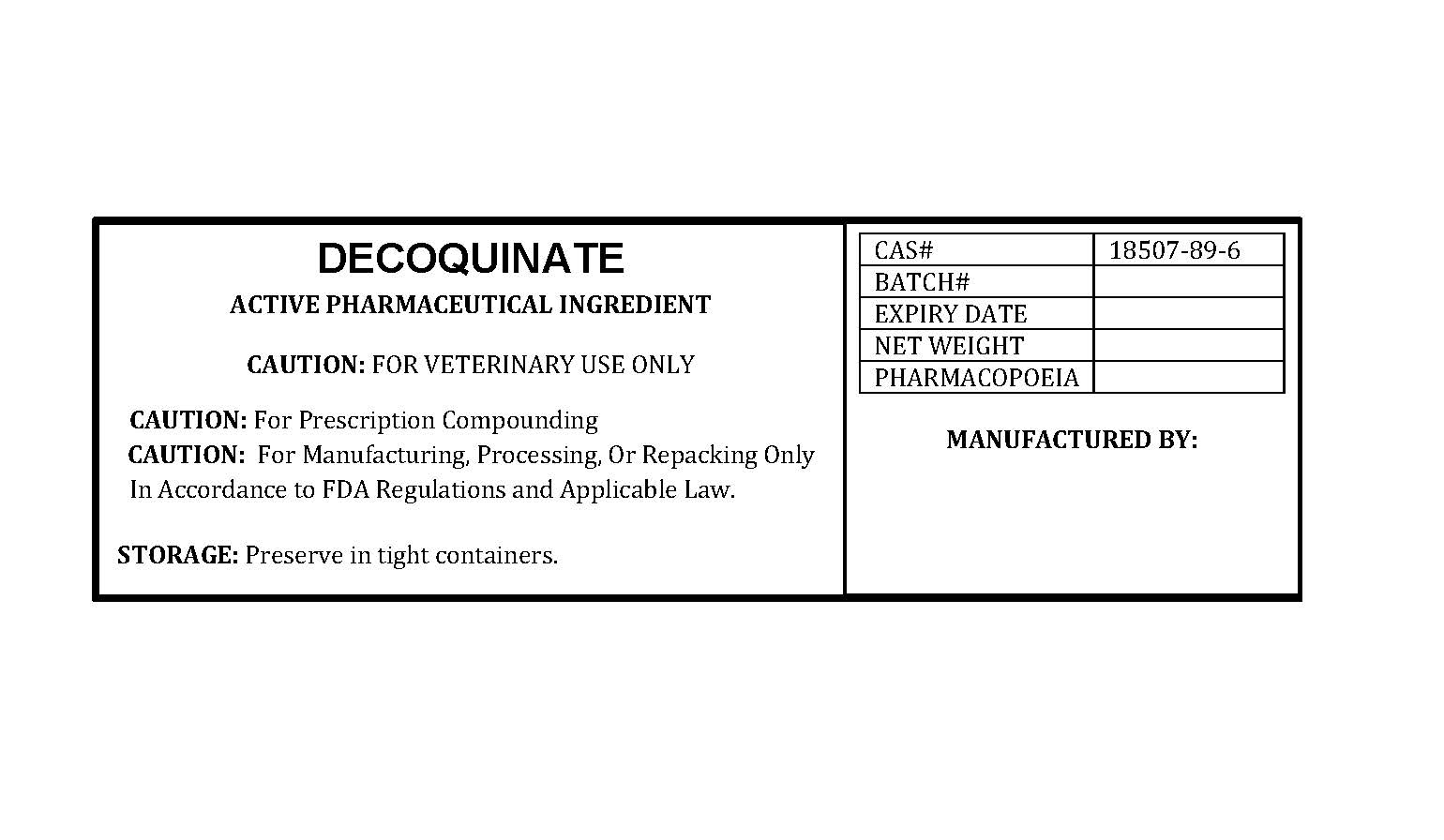 DRUG LABEL: DECOQUINATE
NDC: 86184-063 | Form: POWDER
Manufacturer: MAEDA INC
Category: other | Type: BULK INGREDIENT - ANIMAL DRUG
Date: 20250820

ACTIVE INGREDIENTS: DECOQUINATE 1 g/1 g

DECOQUINATE

PACKAGE LABEL

decoquinatelabelfile.jpg